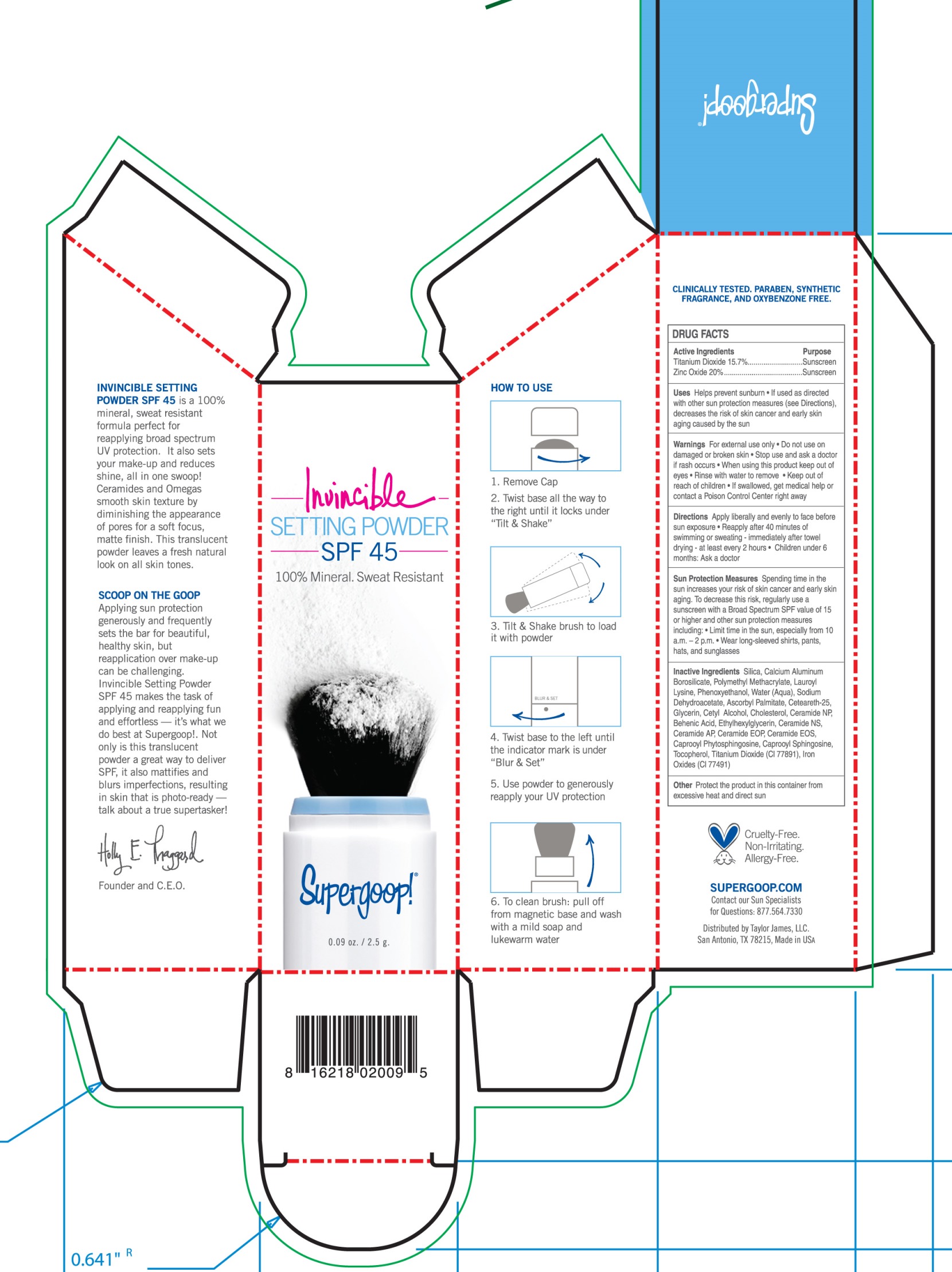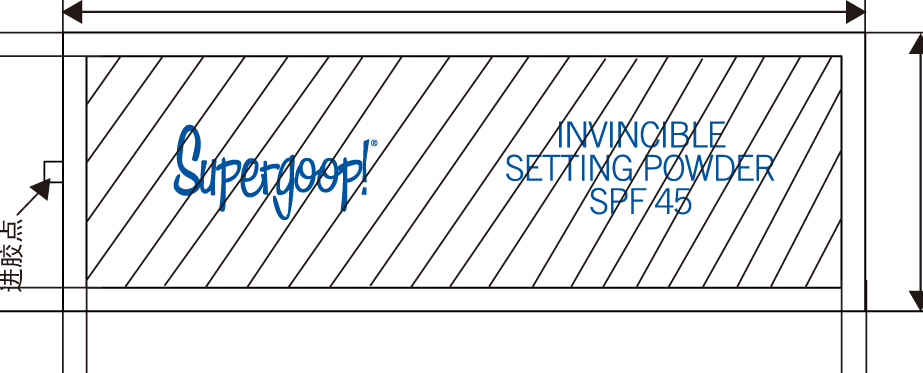 DRUG LABEL: Invincible Setting powder SPF 45
NDC: 75936-105 | Form: POWDER
Manufacturer: TAYLOR JAMES, LTD.
Category: otc | Type: HUMAN OTC DRUG LABEL
Date: 20170113

ACTIVE INGREDIENTS: TITANIUM DIOXIDE 15.7 g/100 g; ZINC OXIDE 20 g/100 g
INACTIVE INGREDIENTS: SILICON DIOXIDE; CALCIUM ALUMINUM BOROSILICATE; POLY(METHYL METHACRYLATE; 450000 MW); LAUROYL LYSINE; PHENOXYETHANOL; WATER; SODIUM DEHYDROACETATE; ASCORBYL PALMITATE; CETEARETH-25; GLYCERIN; CETYL ALCOHOL; CHOLESTEROL; CERAMIDE NP; BEHENIC ACID; ETHYLHEXYLGLYCERIN; CERAMIDE NG; Ceramide AP; CERAMIDE 1; N-HEXANOYLSPHINGOSINE; .ALPHA.-TOCOPHEROL; FERRIC OXIDE RED

Invincible Setting Powder SPF 45

Active ingredients Purpose

Titanium Dioxide 15.7% Sunscreen

Zinc Oxide 20% Sunscreen

PURPOSE

Uses Helps Prevent sunburn

If used as directed with other sun protection measures (see directions), decreases the risk of skin cancer and early skin aging caused by the sun

Keep out of reach of children

Stop use and ask a doctor if rash occurs

Warnings For external use only

Do not on damaged or broken skin

When using this product keep out of eyes

Rinse with water to remove

If swallowed, get medical help or contact a Poison Center right away

DOSAGE AND ADMINISTRATION

Directions Apply liberally and evenly to face before sun exposure

Reapply after 40 minutes of swimming or sweating

immediately after towel drying

at least every 2 hours

Children under 6 months: Ask a doctor

INACTIVE INGREDIENT

Inactive Ingredients Silica, Calcium Aluminum Borosilicate, Polymethyl Methacrylate, Lauroyl Lysine, Phenoxyethanol, Water (Aqua), Sodium Dehydroacetate, Ascorbyl palmitate, Ceteareth-25, Glycerin, Cetyl Alcohol, Cholesterol, Ceramide NP, Behenic Acid, Ethylhexyglycerin, Ceramide NS, Ceramide AP, Ceramide EOP, Ceramide EOS, Caprooyl Pytosphingosine, Caprooyl Sphingosine, Tocopherol, Titanium Dioxide (CI77891), Iron Oxides (CI 77491)

PACKAGE LABEL

Invincible Setting Powder

SPF 45

100% mineral. Sweat Resistant

0.09 oz / 2.5 g